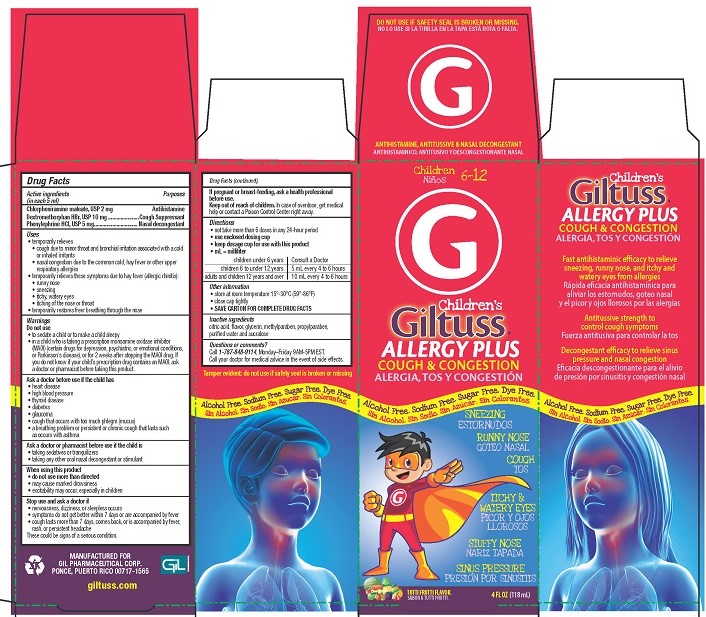 DRUG LABEL: Giltuss Childrens Allergy Plus

NDC: 58552-139 | Form: SOLUTION
Manufacturer: Gil Pharmaceutical Corp
Category: otc | Type: HUMAN OTC DRUG LABEL
Date: 20251009

ACTIVE INGREDIENTS: CHLORPHENIRAMINE MALEATE 2 mg/5 mL; DEXTROMETHORPHAN HYDROBROMIDE 10 mg/5 mL; PHENYLEPHRINE HYDROCHLORIDE 5 mg/5 mL
INACTIVE INGREDIENTS: PROPYLPARABEN; METHYLPARABEN; GLYCERIN; WATER; ANHYDROUS CITRIC ACID; SUCRALOSE

Giltuss Children's Allergy Plus Cough & Congestion

Drug Facts

Active ingredients (in each 5 mL)

Chlorpheniramine maleate USP, 2 mg

Dextromethorphan HBr USP, 10 mg

Phenylephrine HCl USP, 5 mg

Purposes

Antihistamine

Cough Suppressant

Nasal decongestant

Uses

- temporarily relieves
- cough due to minor throat and bronchial irritation associated with a cold or inhaled irritants
- nasal congestion due to the common cold, hay fever or other upper respiratory allergies
- temporarily relieves these symptoms due to hay fever (allergic rhinitis):
- runny nose
- sneezing
- itchy, watery eyes
- itching of the nose or throat
- temporarily restores freer breathing through the nose

Warnings

Do not use

- to sedate a child or to make a child sleepy
- in a child who is taking a prescription monoamine oxidase inhibitor (MAOI) (certain drugs for depression, psychiatric, or emotional conditions, or Parkinson's disease), or for 2 weeks after stopping the MAOI drug. If you do not know if your child's prescription drug contains an MAOI, ask a doctor or pharmacist before taking this product.

Ask a doctor before use if the child has

- heart disease
- high blood pressure
- thyroid disease
- diabetes
- glaucoma
- cough that occurs with too much phlegm (mucus)
- a breathing problem or persistent or chronic cough that lasts such as occurs with asthma

Ask a doctor or pharmacist before use if the child is

- taking sedatives or tranquilizers
- taking any other oral nasal decongestant or stimulant

When using this product

- do not use more than directed
- may cause marked drowsiness
- excitability may occur, especially in children

Stop use and ask a doctor if

- nervousness, dizzyness, or sleepless occurs
- symptoms do not get better within 7 days or are accompanied by a fever
- cough lasts more than 7 days, comes back, or is accompanied by fever, rash or persistent headache.

These could be signs of a serious condition.

PREGNANCY OR BREAST FEEDING

If pregnant or breastfeeding, ask a health professional before use.

Keep out of reach of children.In case of overdose, get medical help or contact a Poison Control Center right away.

Directions

- not take more than 6 doses in any 24-hour period
- use enclosed dosing cup
- keep dosage cup for use with this product
- mL=milliter

children under 6 years | Consult a Doctor
children 6 to under 12 years | 5 mL every 4 to 6 hours
adults and children 12 years and over | 10 mL every 4 to 6 hours

Other information

- store at room temperature 15° - 30°C (59° - 86°F)
- close cap tightly
- SAVE CARTON FOR COMPLETE DRUG FACTS

Inactive ingredients

citric acid, flavor, glycerin, methylparaben, propylparaben, purified water and sucralose

Questions or comments?Call 1-787-848-9114, Monday-Friday 9AM-5PM EST. Call your doctor for medical advice in the event of side effects.

Tamper evident: do not use if safety seal is broken or missing

MANUFACTURED FOR

GIL PHARMACEUTICAL CORP.

PONCE, PUERTO RICO 00717-1565

giltuss.com

PACKAGE LABEL

Children's

Giltuss® ALLERGY PLUS COUGH & CONGESTION

ANTIHISTAMINIC, ANTITUSSIVE, & NASAL DECONGESTANT

Alcohol Free. Sodium Free. Sugar Free. Dye Free.

- SNEEZING
- RUNNY NOSE
- COUGH
- ITCHY & WATERY EYES
- STUFFY NOSE
- SINUS PRESSURE

TUTTI FRUTTI FLAVOR

4 FL OZ (118 mL)